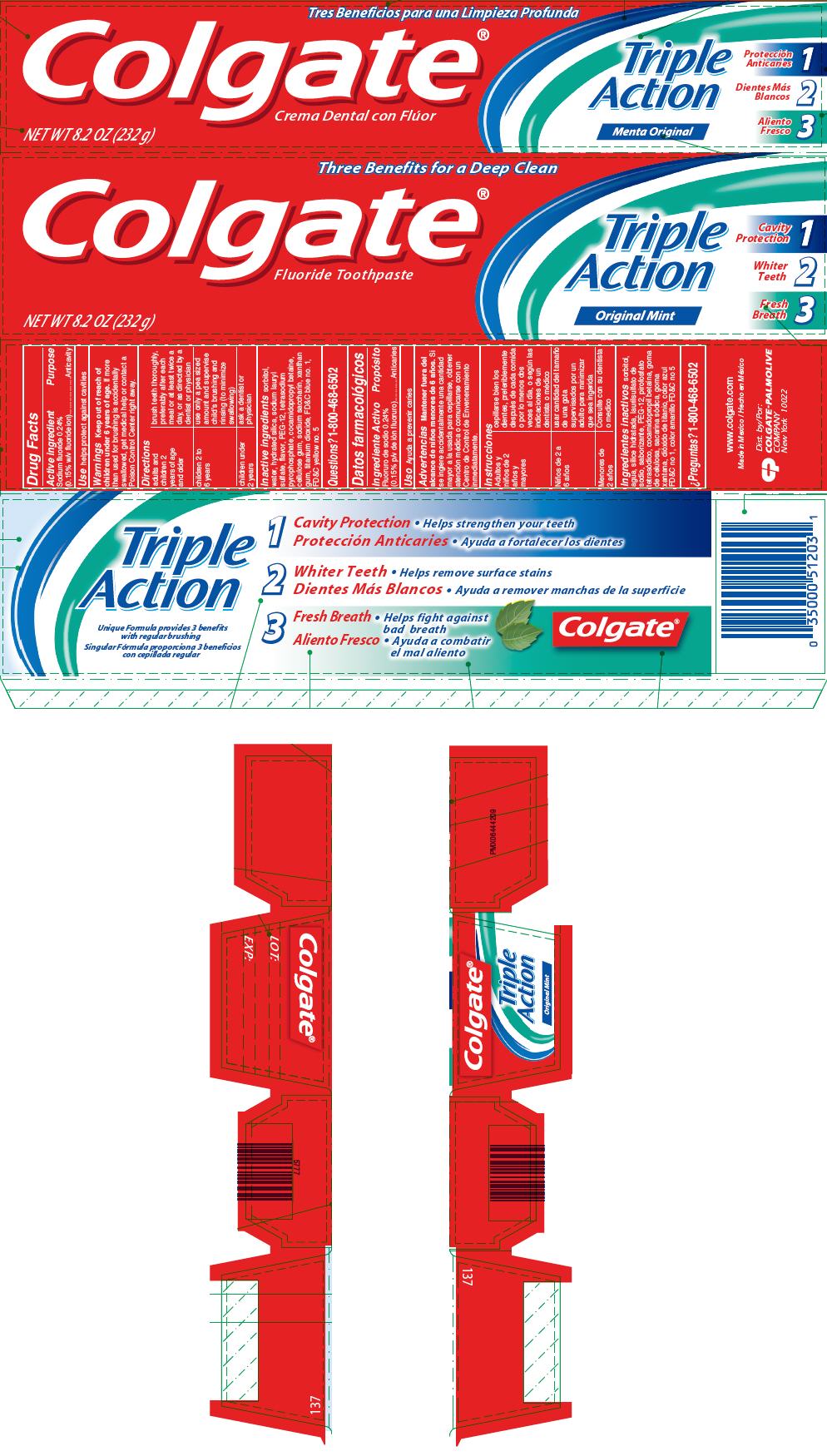 DRUG LABEL: Colgate Triple Action
NDC: 35000-941 | Form: PASTE, DENTIFRICE
Manufacturer: Colgate-Palmolive Company
Category: otc | Type: HUMAN OTC DRUG LABEL
Date: 20191210

ACTIVE INGREDIENTS: SODIUM FLUORIDE 1.1 mg/1 g
INACTIVE INGREDIENTS: HYDRATED SILICA 220 mg/1 g; WATER; SORBITOL; POLYETHYLENE GLYCOL 600; FD&C BLUE NO. 1; SODIUM LAURYL SULFATE; COCAMIDOPROPYL BETAINE; SODIUM PYROPHOSPHATE; CARBOXYMETHYLCELLULOSE SODIUM, UNSPECIFIED; FD&C YELLOW NO. 5; SACCHARIN SODIUM; XANTHAN GUM; TITANIUM DIOXIDE

Colgate® Triple Action Fluoride Toothpaste

Drug Facts

Active ingredient

Sodium fluoride 0.24% (0.15% w/v fluoride ion)

Purpose

Anticavity

Use

helps protect against cavities

Warnings

Keep out of reach of children under 6 years of age. If more than used for brushing is accidentally swallowed, get medical help or contact a Poison Control Center right away.

Directions

adults and children 2 years of age and older | brush teeth thoroughly, preferably after each meal or at least twice a day, or as directed by a dentist or physician
children 2 to 6 years | use only a pea sized amount and supervise child's brushing and rinsing (to minimize swallowing)
children under 2 years | ask a dentist or physician

Inactive ingredients

sorbitol, water, hydrated silica, sodium lauryl sulfate, flavor, PEG-12, tetrasodium pyrophosphate, cocamidopropyl betaine, cellulose gum, sodium saccharin, xanthan gum, titanium dioxide, FD&C blue no. 1, FD&C yellow no. 5

Questions?

1-800-468-6502

Dist. by:
COLGATE-PALMOLIVE
COMPANY
New York 10022

PRINCIPAL DISPLAY PANEL - 232 g Tube Carton

Three Benefits for a Deep Clean

Colgate®
Fluoride Toothpaste

NET WT 8.2 OZ (232 g)

Triple
Action

Original Mint

Cavity
Protection
1

Whiter
Teeth
2

Fresh
Breath
3